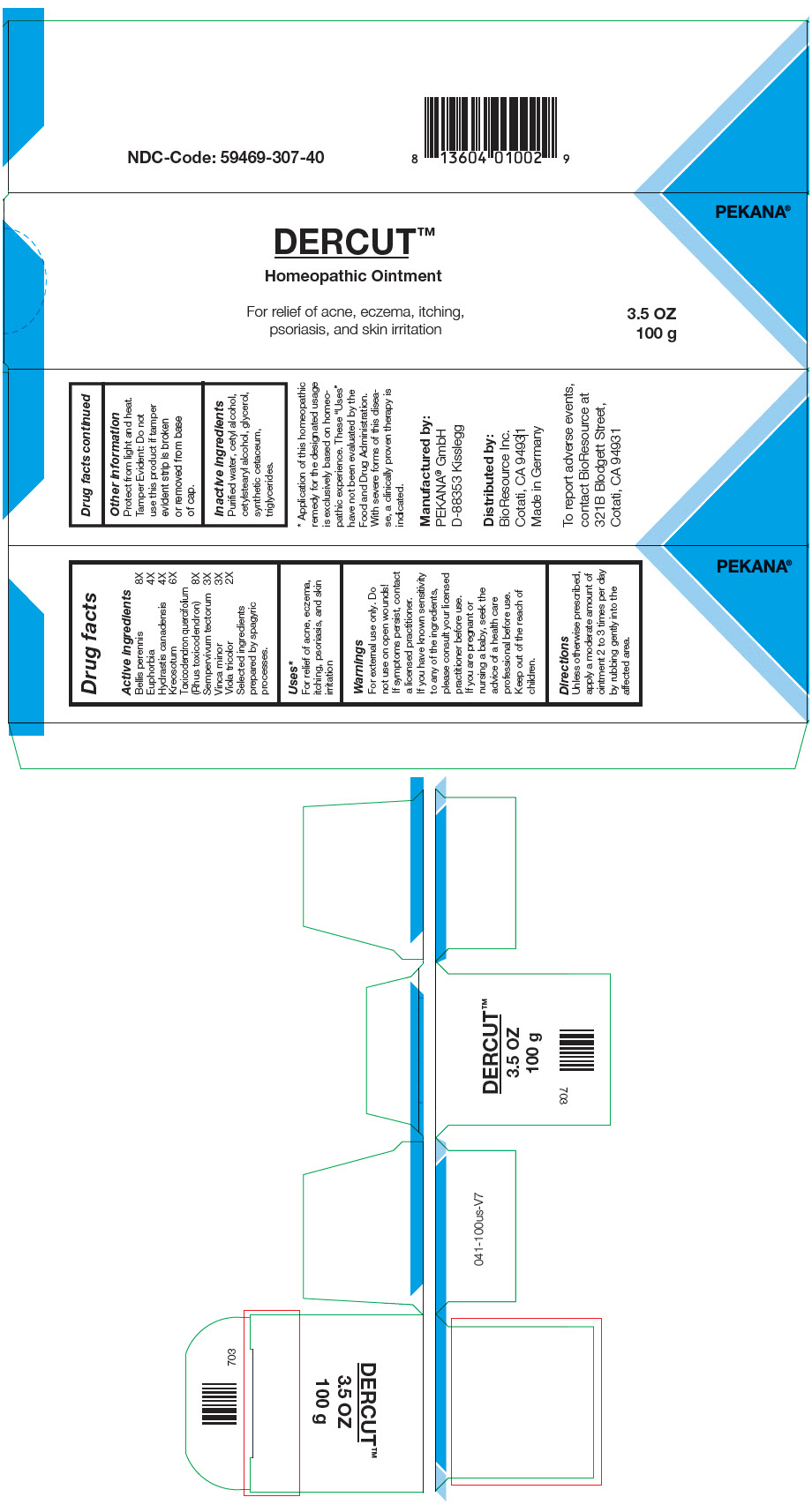 DRUG LABEL: DERCUT
NDC: 59469-307 | Form: OINTMENT
Manufacturer: PEKANA Naturheilmittel GmbH
Category: homeopathic | Type: HUMAN OTC DRUG LABEL
Date: 20220114

ACTIVE INGREDIENTS: EUPHORBIA RESINIFERA RESIN 4 [hp_X]/100 g; GOLDENSEAL 4 [hp_X]/100 g; WOOD CREOSOTE 6 [hp_X]/100 g; TOXICODENDRON PUBESCENS SHOOT 8 [hp_X]/100 g; Sempervivum tectorum Leaf 3 [hp_X]/100 g; BELLIS PERENNIS WHOLE 8 [hp_X]/100 g; PERVINCA MINOR WHOLE 3 [hp_X]/100 g; VIOLA TRICOLOR WHOLE 2 [hp_X]/100 g
INACTIVE INGREDIENTS: MEDIUM-CHAIN TRIGLYCERIDES; CETOSTEARYL ALCOHOL; Cetyl Alcohol; SPERMACETI; Glycerin; WATER; Alcohol

DERCUT™

Drug facts

Active ingredients
Bellis perennis | 8X
Euphorbia | 4X
Hydrastis canadensis | 4X
Kreosotum | 6X
Toxicodendron quercifolium (Rhus toxicodendron) | 8X
Sempervivum tectorum | 3X
Vinca minor | 3X
Viola tricolor | 2X

Selected ingredients prepared by spagyric processes.

Uses [Application of this homeopathic remedy for the designated usage is exclusively based on homeopathic experience. These "Uses" have not been evaluated by the Food and Drug Administration. With severe forms of this disease, a clinically proven therapy is indicated.]

PURPOSE

For relief of acne, eczema, itching, psoriasis, and skin irritation

Warnings

For external use only. Do not use on open wounds!

If symptoms persist, contact a licensed practitioner.

If you have known sensitivity to any of the ingredients, please consult your licensed practitioner before use.

If you are pregnant or nursing a baby, seek the advice of a health care professional before use.

Keep out of the reach of children.

Directions

Unless otherwise prescribed, apply a moderate amount of ointment 2 to 3 times per day by rubbing gently into the affected area.

Other information

Protect from light and heat.

Tamper Evident

Do not use this product if tamper evident strip is broken or removed from base of cap.

Inactive ingredients

Purified water, cetyl alcohol, cetylstearyl alcohol, glycerol, synthetic cetaceum, triglycerides.

Manufactured by:
PEKANA® GmbH
D-88353 Kisslegg

Distributed by:
BioResource Inc.
Cotati, CA 94931

PRINCIPAL DISPLAY PANEL - 100 g Tube Box

DERCUT™
Homeopathic Ointment

For relief of acne, eczema, itching,
psoriasis, and skin irritation

3.5 OZ
100 g

PEKANA®